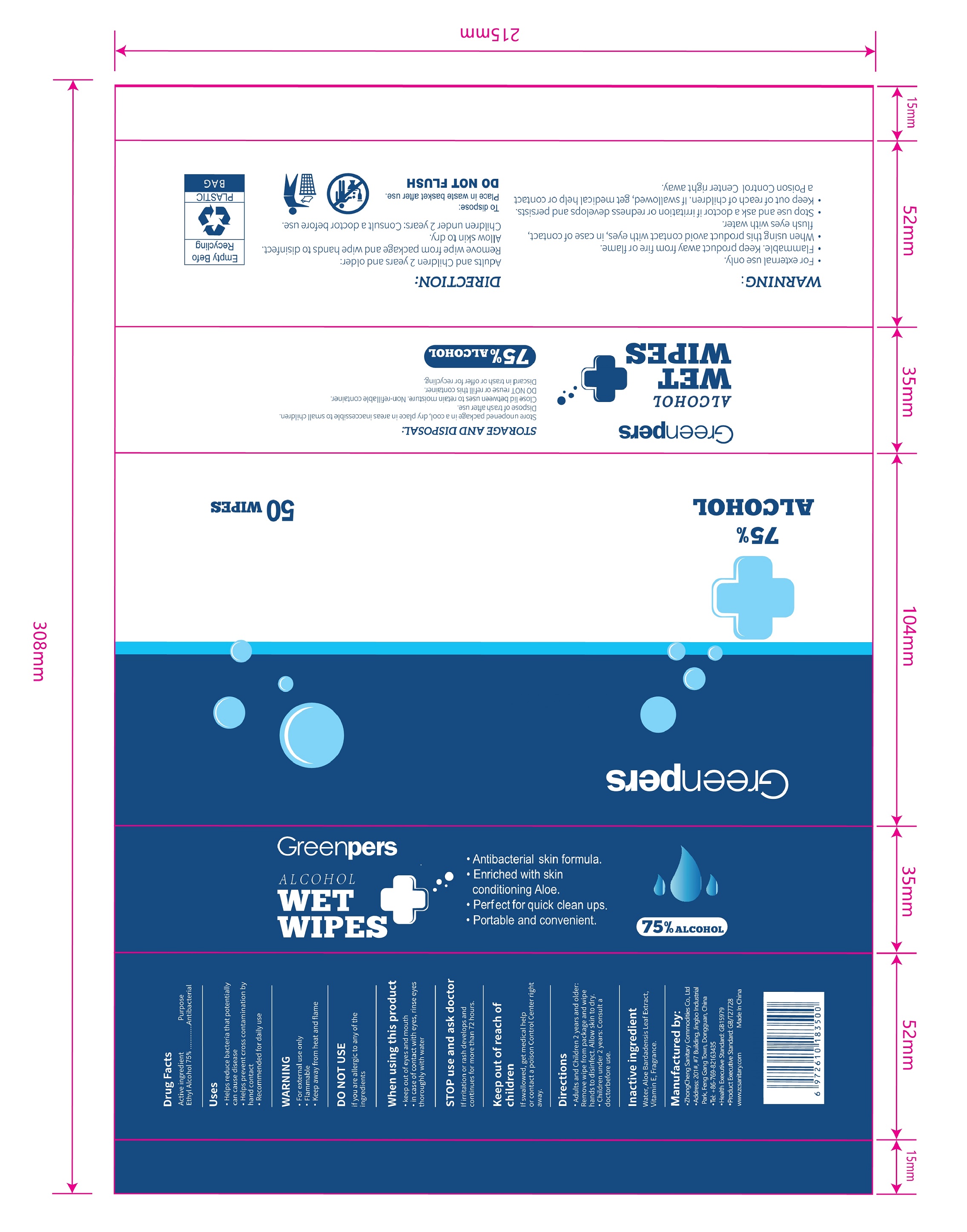 DRUG LABEL: ALCOHOL WIPES
NDC: 55482-050 | Form: CLOTH
Manufacturer: Dongguan Zhongcheng Sanitary Commodities Co., Ltd.
Category: otc | Type: HUMAN OTC DRUG LABEL
Date: 20210316

ACTIVE INGREDIENTS: ALCOHOL 75 mL/100 mL
INACTIVE INGREDIENTS: .ALPHA.-TOCOPHEROL; ALOE VERA LEAF; BERGAMOT OIL; WATER

55482-050-01 50wipes 20200930

Active Ingredient(s)

Alcohol 75% v/v. Purpose: Antibacterial;

Purpose

Antibacterial, Alcohol Wipes

Use

- Helps reduce bacteria that potentially can cause disease.
- Helps prevent cross contamination by hand contact.
- Recommended for daily use.

Warnings

- For external use only.
- Flammable.
- Keep away from heat or flame

- DO NOT USE if you are allergic to any of the ingredients

When using this product

- keep out of eyes and mouth.
- incase of contact with eyes, rinse eyes thoroughly with water.

Stop use and ask a doctor if irritation or rash develops and continues for more than 72 hours.

Keep out of reach of children. If swallowed, get medical help or contact a Poison Control Center right away.

Directions

- Adults and Children 2 years and older: Remove wipe from package and wipe hands to disinfect. Allow skin to dry.
- Children under 2 years: Consult a doctor before use.

Other information

- Store between 15-30C (59-86F)
- Avoid freezing and excessive heat above 40C (104F)

Inactive ingredients

Water, Aloe Bardadensis Leaf Extract, Vitamin E, Fragrance.

Package Label - Principal Display Panel

50 wips in 1 canister NDC: 55482-050-01